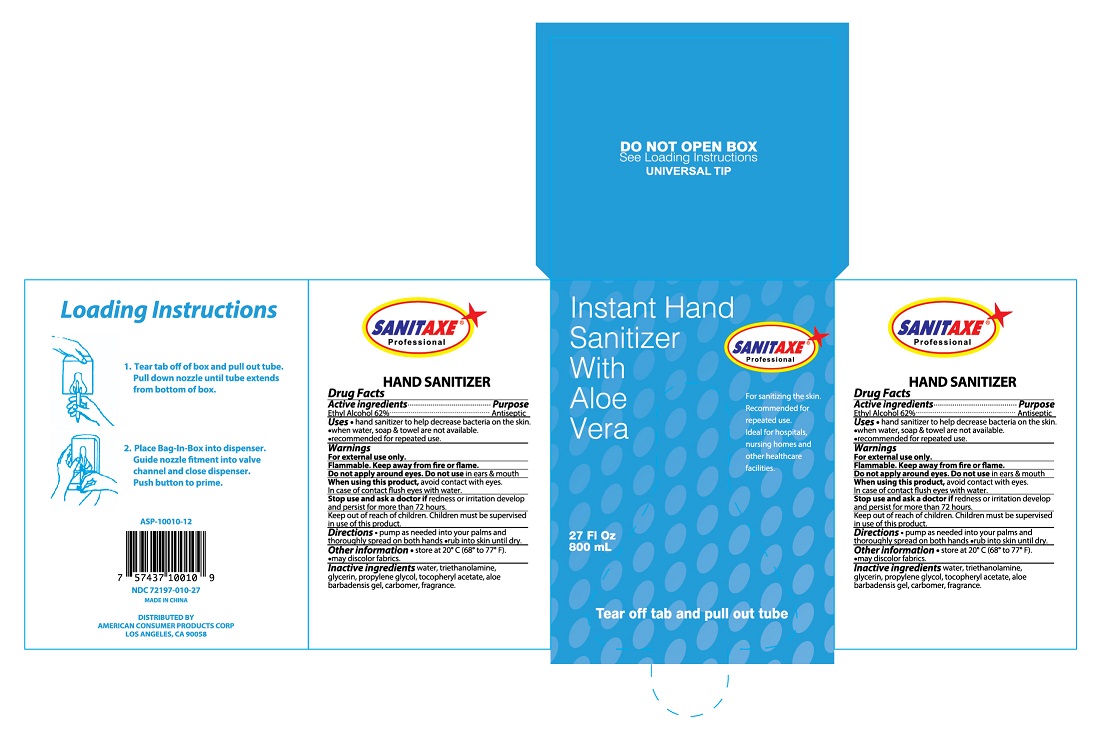 DRUG LABEL: SANITAXE 27 OZ INSTANT HAND SANITIZER WITH ALOE VERA
NDC: 72197-010 | Form: GEL
Manufacturer: American Consumer Products Corp
Category: otc | Type: HUMAN OTC DRUG LABEL
Date: 20190820

ACTIVE INGREDIENTS: ALCOHOL 62 mL/100 mL
INACTIVE INGREDIENTS: PROPYLENE GLYCOL 2-(2-METHYLBUTYRATE); WATER; .ALPHA.-TOCOPHEROL ACETATE, D-; TRIETHANOLAMINE 2-CYCLOHEXYL-4,6-DINITROPHENOLATE; CARBOMER HOMOPOLYMER TYPE C; ALOE ARBORESCENS WHOLE; GLYCERIN

Sanitaxe 27 OZ Instant Hand Sanitizer With Aloe Vera

Active Ingredient

Active Ingredients: Ethyl Alcohol 62%

Purpose

Purpose: Antiseptic

Uses - Hand sanitizer to help decrease bacteria on the skin. When water, soap & towel are not available

Recommended for repeated use.

Warnings

Warnings - For External use only.

Flammable. Keep away from fire or flame.

Stop Use

Stop use and ask a doctor if redness or irritation develop and persist for more than 72 hours.

Keep out of reach of children. Children must be surpervised in use of this product.

Inactive Ingredients

Inactive ingredients - water, triethanolamine, glycerin, propylene glycol, tocopheryl acetate, aloe barbadensis gel, carbomer, fragrance.

Directions

Directions - pump as needed into your palms and thoroughly spread on both hands. Rub into skin until dry.

Indications & Usage Section

When using this product, avoid contact with eyes. In case of contact flush eyes with water.

Other Information

Other information - store at 20ºC (68º to 77º F). May discolor fabric.